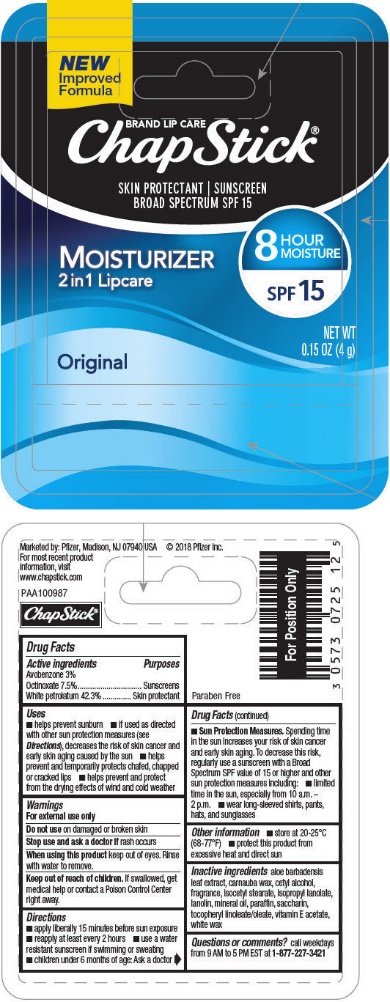 DRUG LABEL: Chapstick Moisturizer Original
NDC: 0573-0725 | Form: STICK
Manufacturer: Haleon US Holdings LLC
Category: otc | Type: HUMAN OTC DRUG LABEL
Date: 20240322

ACTIVE INGREDIENTS: AVOBENZONE 30 mg/1 g; OCTINOXATE 75 mg/1 g; PETROLATUM 423 mg/1 g
INACTIVE INGREDIENTS: ALOE VERA LEAF; CARNAUBA WAX; CETYL ALCOHOL; .ALPHA.-TOCOPHEROL LINOLEATE, D-; ISOCETYL STEARATE; LANOLIN; MINERAL OIL; PARAFFIN; SACCHARIN; .ALPHA.-TOCOPHEROL ACETATE; WHITE WAX

Drug Facts

Active ingredients

Avobenzone 3%

Octinoxate 7.5%

White petrolatum 42.3%

Purposes

Sunscreens

Skin protectant

Uses

- helps prevent sunburn
- if used as directed with other sun protection measures (see Directions), decreases the risk of skin cancer and early skin aging caused by the sun
- helps prevent and temporarily protects chafed, chapped or cracked lips
- helps prevent and protect from the drying effects of wind and cold weather

Warnings

For external use only

Do not use on damaged or broken skin

Stop use and ask a doctor if rash occurs

When using this product keep out of eyes. Rinse with water to remove.

Keep out of reach of children. If swallowed, get medical help or contact a Poison Control Center right away.

Directions

- apply liberally 15 minutes before sun exposure
- reapply at least every 2 hours
- use a water resistant sunscreen if swimming or sweating
- children under 6 months of age: Ask a doctor
- Sun Protection Measures. Spending time in the sun increases your risk of skin cancer and early skin aging. To decrease this risk, regularly use a sunscreen with a Broad Spectrum SPF value of 15 or higher and other sun protection measures including:
  - Limit time in the sun, especially from 10 a.m. – 2 p.m.
  - Wear long-sleeved shirts, pants, hats, and sunglasses

Other information

- store at 20-25°C (68-77°F)
- protect the product from excessive heat and direct sun

Inactive ingredients

aloe barbadensis leaf extract, carnauba wax, cetyl alcohol, fragrance, isocetyl stearate, isopropyl lanolate, lanolin, mineral oil, paraffin, saccharin, tocopheryl linoleate/oleate, vitamin E acetate, white wax

Questions or comments?

call weekdays from 8 AM to 6 PM EST at 1-800-245-1040

Additional information

Distributed by: GSK Consumer Healthcare, Warren, NJ 07059

For most recent product information, visit www.chapstick.com

Trademarks are owned by or licensed to the

GSK group of companies.

©2023 GSK or licensor.

Paraben Free

Moisturizer Original

PRINCIPAL DISPLAY PANEL

NEW
Improved
Formula

BRAND LIP CARE
ChapStick®

SKIN PROTECTANT | SUNSCREEN
BROAD SPECTRUM SPF 15

MOISTURIZER
2 in 1 Lipcare

8
HOUR
MOISTURE

SPF 15

Original

NET WT 0.15 OZ (4 g)